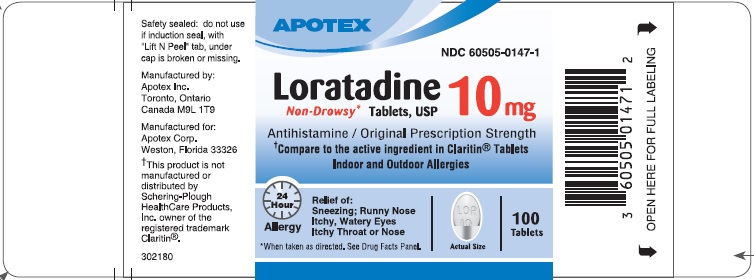 DRUG LABEL: Loratadine
NDC: 60505-0147 | Form: TABLET
Manufacturer: Apotex Corp.
Category: otc | Type: HUMAN OTC DRUG LABEL
Date: 20250922

ACTIVE INGREDIENTS: LORATADINE 10 mg/1 1
INACTIVE INGREDIENTS: SILICON DIOXIDE; CROSCARMELLOSE SODIUM; LACTOSE MONOHYDRATE; MAGNESIUM STEARATE; MICROCRYSTALLINE CELLULOSE

Loratadine Tablet 10 mg

Drug Facts

Active ingredient (in each tablet)

Loratadine 10 mg

Purpose

Antihistamine

Uses

temporarily relieves these symptoms due to hay fever or other upper respiratory allergies:

- runny nose
- sneezing
- itchy, watery eyes
- itching of the nose or throat

Warnings

Do not use if you have ever had an allergic reaction to this product or any of its ingredients.

Ask a doctor before use if you have liver or kidney disease. Your doctor should determine if you need a different dose.

When using this product do not take more than directed. Taking more than directed may cause drowsiness.

Stop use and ask a doctor if an allergic reaction to this product occurs. Seek medical help right away.

WARNINGS

If pregnant or breast-feeding, ask a health professional before use.

Keep out of reach of children. In case of overdose, get medical help or contact a Poison Control Center right away.

Directions

adults and children 6 years and over | 1 tablet daily; not more than 1 tablet in 24 hours
children under 6 years of age | ask a doctor
consumers with liver or kidney disease | ask a doctor

Other information

- safety sealed: do not use if induction seal, with "Lift N Peel" tab, under cap is broken or missing
- store between 2°C and 30°C (36°F and 86°F)
- protect from excessive moisture

Inactive ingredients

colloidal silicon dioxide, croscarmellose sodium, lactose monohydrate, magnesium stearate, microcrystalline cellulose

Questions or comments?

Call 1-800-706-5575, weekdays, 8:30 am - 5:00 pm Eastern Standard Time

Manufactured by: | Manufactured for:
Apotex Inc. | Apotex Corp.
Toronto, Ontario | Weston, Florida
Canada M9L 1T9 | 33326

Revised: August 2018

PRINCIPAL DISPLAY PANEL - 10 mg

APOTEX CORP. NDC 60505-0147-1

Loratadine Tablets 10 mg

Non-Drowsy*

Antihistamine/Original Prescription Strength

†Compare to the active ingredient in Claritin® Tablets

Indoor & Outdoor Allergies

24 hour

Relief of

- Sneezing
- Runny Nose
- Itchy, Watery Eyes
- Itchy Throat or Nose